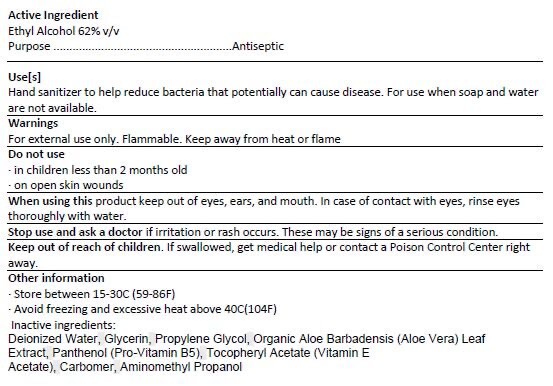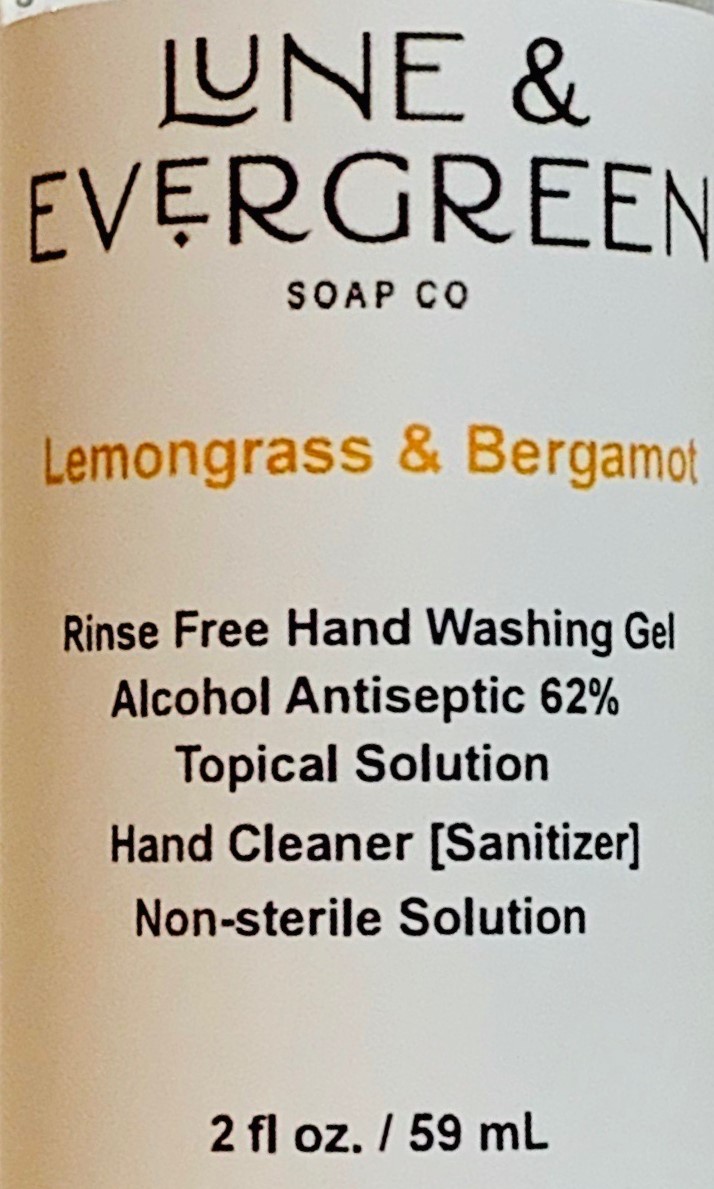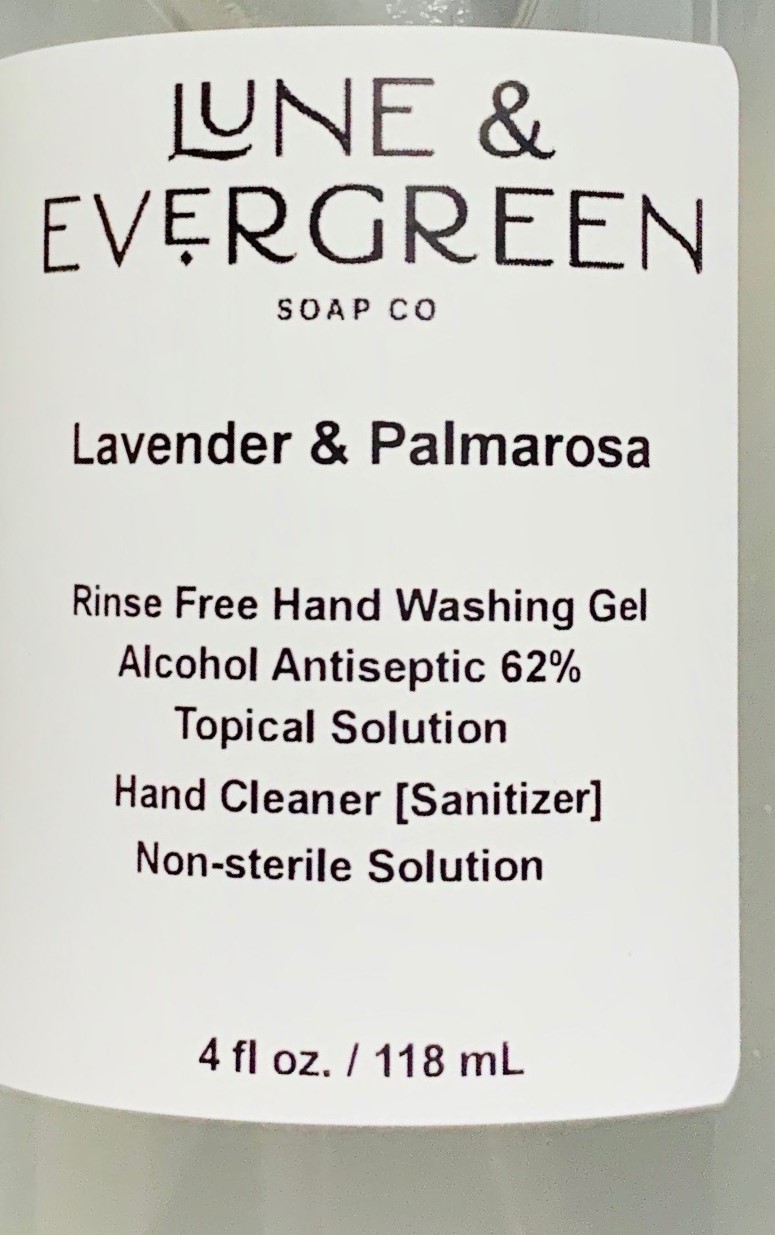 DRUG LABEL: Rinse Free Hand Cleanser
NDC: 73909-0918 | Form: GEL
Manufacturer: Lune & Evergreen Soap Company LLC
Category: otc | Type: HUMAN OTC DRUG LABEL
Date: 20200427

ACTIVE INGREDIENTS: ALCOHOL 62 mL/100 mL
INACTIVE INGREDIENTS: GLYCERIN 1.45 mL/100 mL; PROPYLENE GLYCOL 0.125 mL/100 mL; WATER; HYDROXYPROPYL CELLULOSE (90000 WAMW) 1.25 mL/100 mL

Rinse Free Hand Wash

This is a Rinse free hand cleanser repackaged/labeled.

The hand sanitizer is manufactured using only the following United States Pharmacopoeia (USP) grade ingredients in the preparation of the product (percentage in final product formulation) consistent with Center for Disease Control recommendations:

1. Cleaning hands at key times with soap and water or hand sanitizer that contains at least 60% alcohol is one of the most important steps you can take to avoid getting sick and spreading germs to those around you.

The firm does not add other active ingredients. Any additional ingredients added have been precisly measured and do not drop active ingredient below 62% Ethyl Alcohol, and does not impact the quality and potency of the product.

Active Ingredient(s)

Alcohol 62% v/v. Purpose: Antiseptic

Purpose

Antiseptic, Hand Sanitizer

Use

Hand Sanitizer to help reduce bacteria that potentially can cause disease. For use when soap and water are not available.

Warnings

For external use only. Flammable. Keep away from heat or flame

Do not use

- in children less than 2 months of age
- on open skin wounds

When using this product keep out of eyes, ears, and mouth. In case of contact with eyes, rinse eyes thoroughly with water.
Stop use and ask a doctor if irritation or rash occurs. These may be signs of a serious condition.
Keep out of reach of children. If swallowed, get medical help or contact a Poison Control Center right away.

Stop use and ask a doctor if irritation or rash occurs. These may be signs of a serious condition.

Keep out of reach of children. If swallowed, get medical help or contact a Poison Control Center right away.

Directions

- Place enough product on hands to cover all surfaces. Rub hands together until dry.
- Supervise children under 6 years of age when using this product to avoid swallowing.

Other information

- Store between 15-30C (59-86F)
- Avoid freezing and excessive heat above 40C (104F)

Inactive ingredients

glycerin, Deionized Water, Propylene Glycol, Hydroxypropylcellulose, Lauryl Lactate, Myristyl Lactate, Cetyl Lactate, Organic Aloe Barbadensis (Aloe Vera) Leaf Extract, Panthenol (Pro-Vitamin B5), Tocopheryl Acetate (Vitamin E Acetate)

Package Label - Principal Display Panel

118 mL NDC: 73909-0918-1

59 mL 73909-0918-2

Drug Facts label